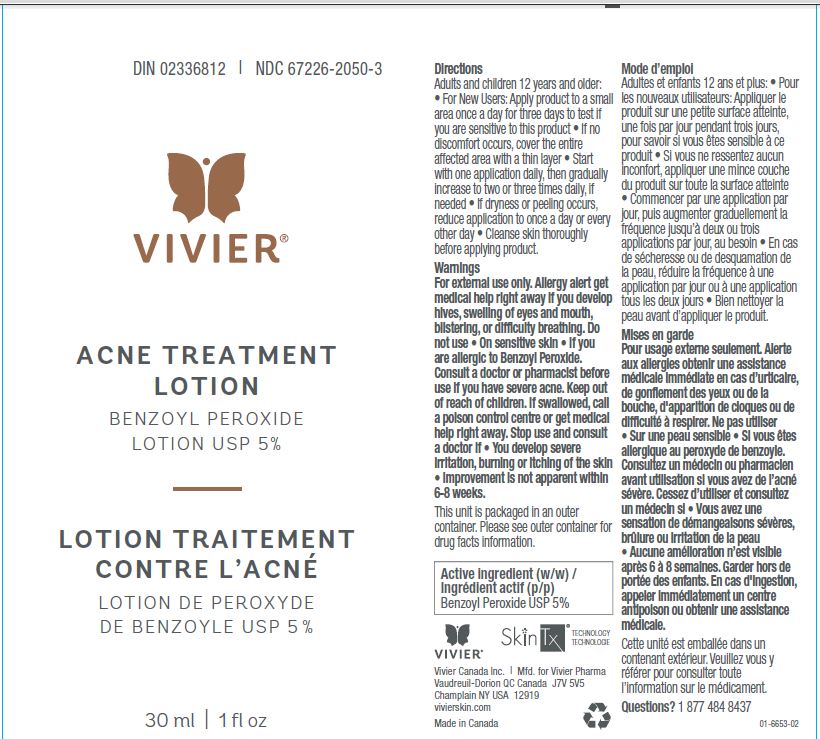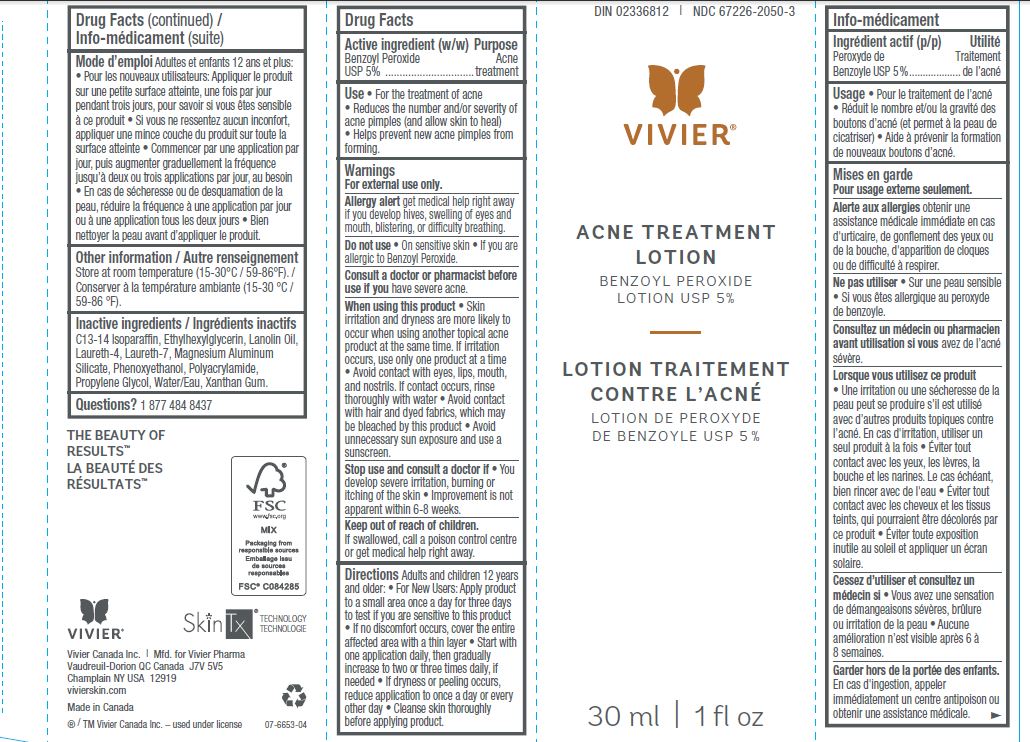 DRUG LABEL: Acne Treatment
NDC: 67226-2050 | Form: LOTION
Manufacturer: Vivier Pharma, Inc.
Category: otc | Type: HUMAN OTC DRUG LABEL
Date: 20231027

ACTIVE INGREDIENTS: BENZOYL PEROXIDE 50 mg/1 mL
INACTIVE INGREDIENTS: C13-14 ISOPARAFFIN; ETHYLHEXYLGLYCERIN; LANOLIN OIL; LAURETH-4; LAURETH-7; MAGNESIUM ALUMINUM SILICATE; PHENOXYETHANOL; PROPYLENE GLYCOL; WATER; XANTHAN GUM

Acne Treatment Lotion Benzoyl Peroxide Lotion USP 5%

Active Ingredient

Benzoyl Peroxide 5%

Purpose

Acne Treatment

Use

For the treatment of acne. Dries, clears and helps keep skin clear of new acne pimples, blackheads and whiteheads.

Warnings

For external use only

Ask a doctor before use if you are

- using other topical acne medications at the same time or immediately following use of this product may increase dryness or irritation of the skin. If this occurs, only one medication should be used unless directed by a doctor.

Keep out of reach of children.

If swallowed, get medical help or contact a Poison Control Center right away.

Do not use if you

- have very sensitive skin.
- are sensitive to Benzoyl Peroxide.

When using this product

- avoid unnecessary sun exposure and use a sunscreen
- avoid contact with eyes, lips, and mouth
- avoid contact with hair and dyed fabrics, which may be bleached by this product
- skin irritation may occur, characterized by redness, burning, itching, peeling, or possibly swelling. Irritation may be reduced by using the product less frequently or in a lower oncentration.

Stop use and ask a doctor if

- irritation becomes severe.

Directions

- Wash hands with a non-medicated soap (contains no Benzoyl Peroxide).
- Cleanse and dry face thoroughly 5 minutes before use.
- Using fingertips apply evenly to affected areas.
- Use both morning and night or as directed by a physician.
- If dryness or peeling occurs, reduce application to once a day or every other day.
- Fair- skinned individuals should begin with one application.
- For more severe cases, and/or if substantial improvement is not apparent within 3 to 4 weeks, consult a health care practitioner.

Inactive Ingredients

C13-14 Isoparaffin, Ethylhexylglycerin, Lanolin Oil, Laureth-4, Laureth-7, Magnesium Aluminum Silicate, Phenoxyethanol, Polyacrylamide, Propylene Glycol, Water/Eau, Xanthan Gum.

Other Information

- store at room temperature (59-86°F / 15-30°C)